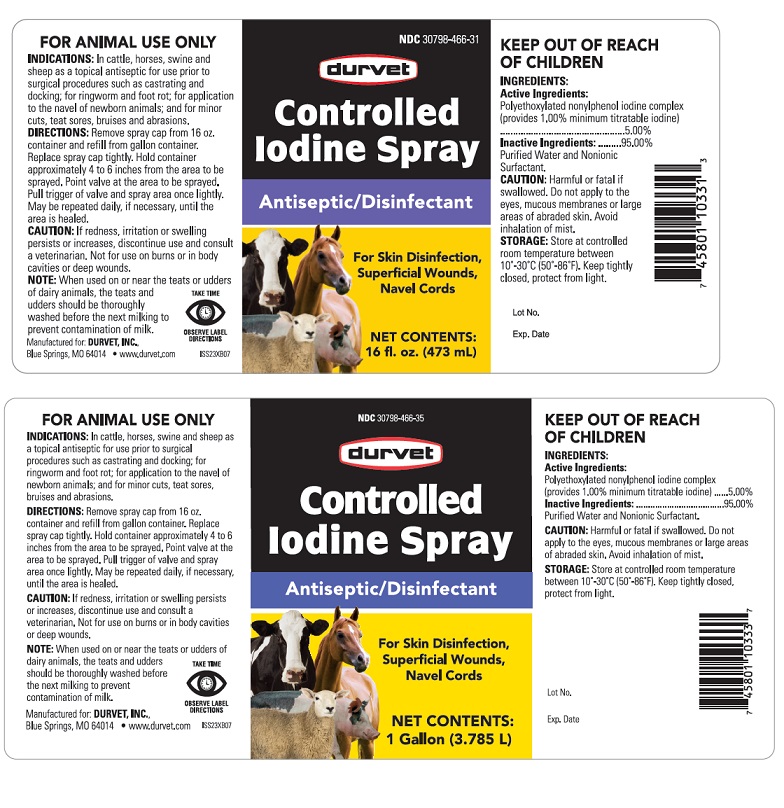 DRUG LABEL: Controlled Iodine
NDC: 30798-466 | Form: SOLUTION
Manufacturer: Durvet Inc
Category: animal | Type: OTC ANIMAL DRUG LABEL
Date: 20241024

ACTIVE INGREDIENTS: IODINE 0.01 mg/1 mL
INACTIVE INGREDIENTS: WATER 0.99 mg/1 mL

INDICATIONS AND USAGE

Controlled Iodine Spray

Antiseptic/Disinfectant

For Skin Disinfection, Superficial Wounds, Navel Cords

FOR ANIMAL USE ONLY

KEEP OUT OF REACH OF CHILDREN

INDICATIONS: In cattle, horses, swine and sheep as a topical antiseptic for use prior to surgical procedures such as castraing and docking; for ringworms and foot rot; for application to the naveal of newborn animals; and for minor cuts, teat sores, bruises and abraissions.

DIRECTIONS:

Remove spray cap from 16 oz. container and refill from gallon container. Replace spray cap tightly. Hold container approximately 4 to 6 inches from the area to be sprayed. Point valve at the area to be sprayed. Pull trigger of valve and spray area once lightly. May be repeated daily, if necessary, until the area is healed.

CAUTION:

If redness, irritation or swelling persists or increases, discontinue use and consult a veterinarian. Not for use on burns or in body cavities or deep wounds.

NOTE: When used on or near the teats or udders of dairy animals, the teats and udders should be thoroughly washed before the next milking to prevent contamination of the milk.

INGREDIENTS:

Active Ingredients:

Polyethoxylated nonylpenol iodine complex (provides 1.00% minimum titratable iodine).....5.00%

Inactive Ingredients:

Purified Water and Nonionic Surfactant...............................................................................95.00%

STORAGE AND HANDLING

CAUTION: Harmful or fatal if swallowed. Do not apply to the eyes, mucous membraines or large areas of abraided skin. Avoid inhalation of mist.

STORAGE: Store at controlled room temperature between 10°-30°C (50°-86°F) Keep tightly closed, protect from light.